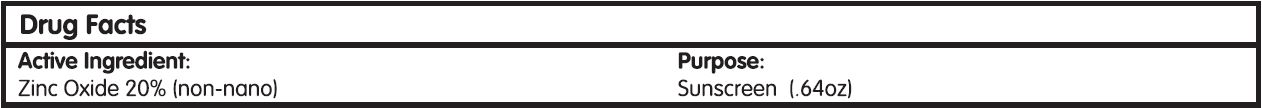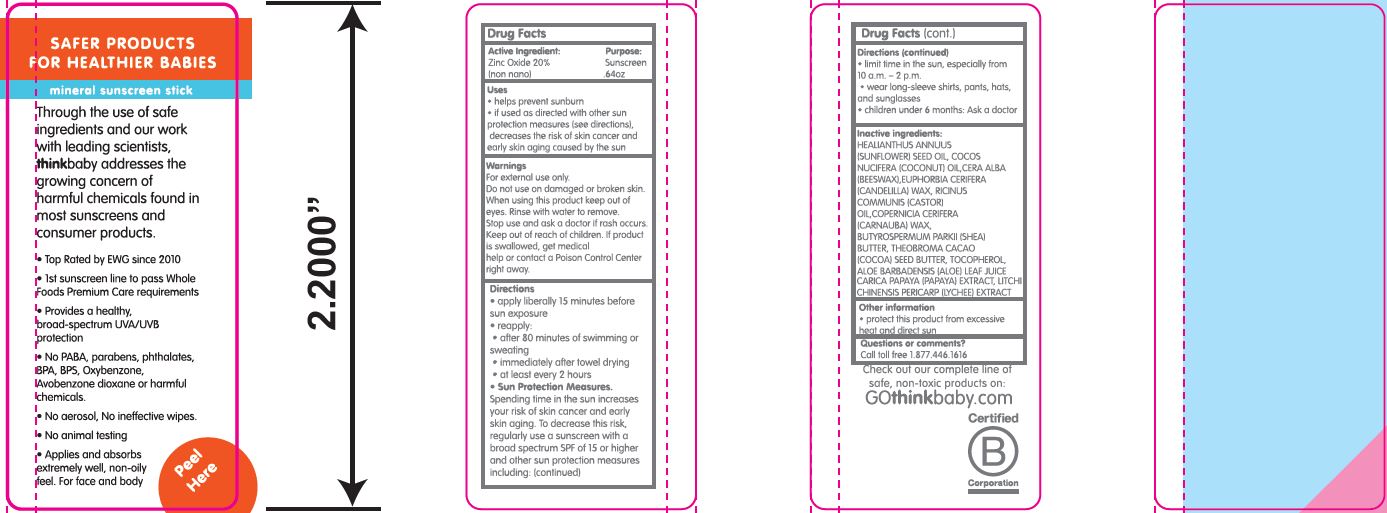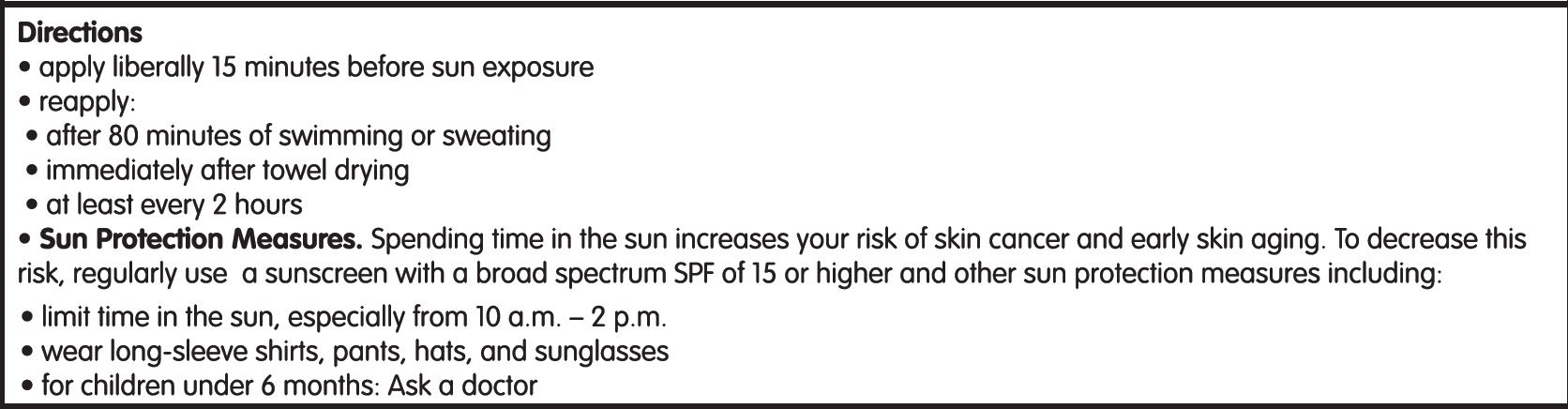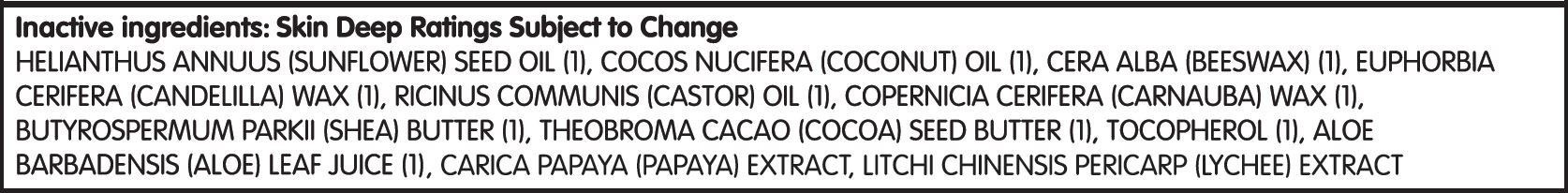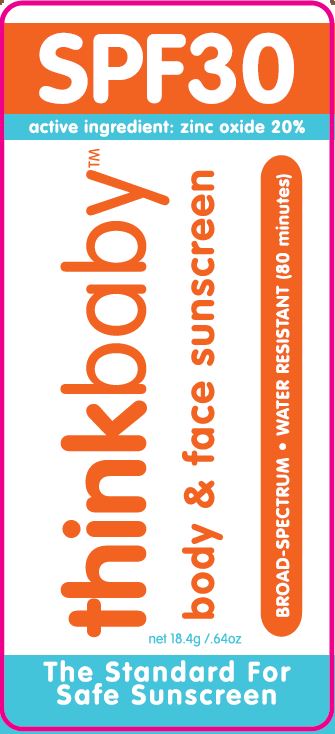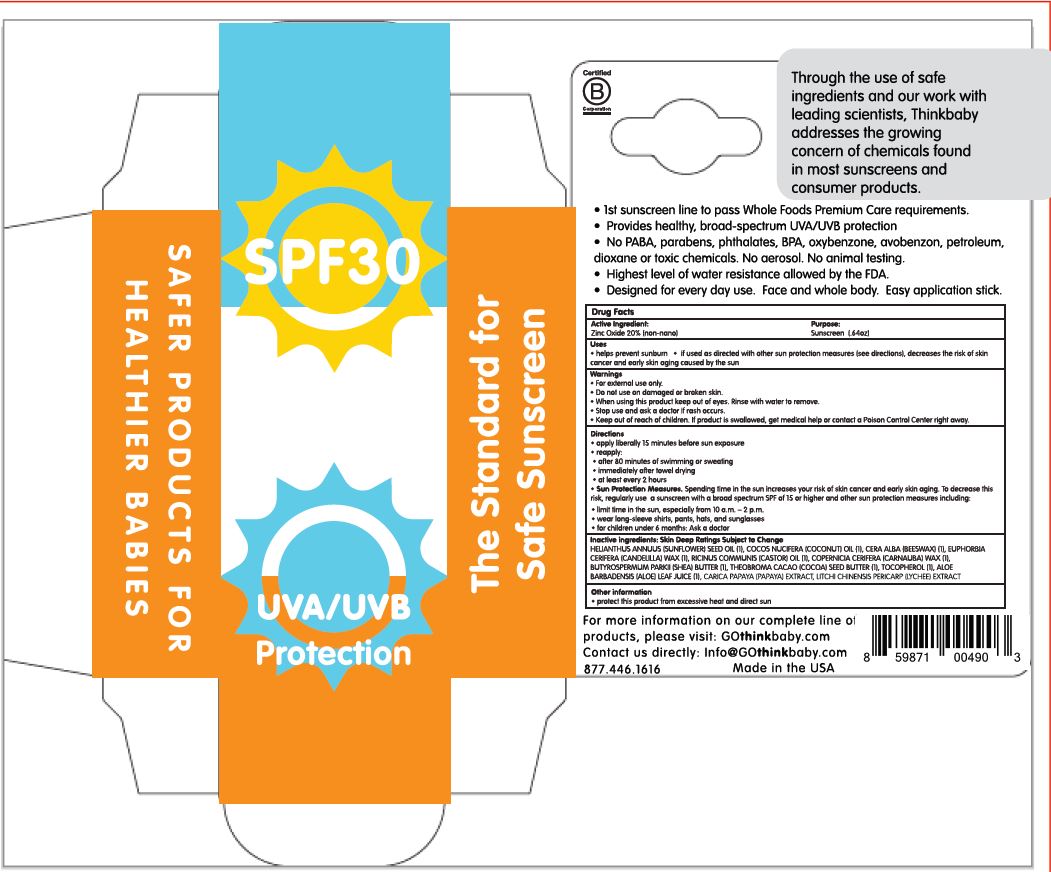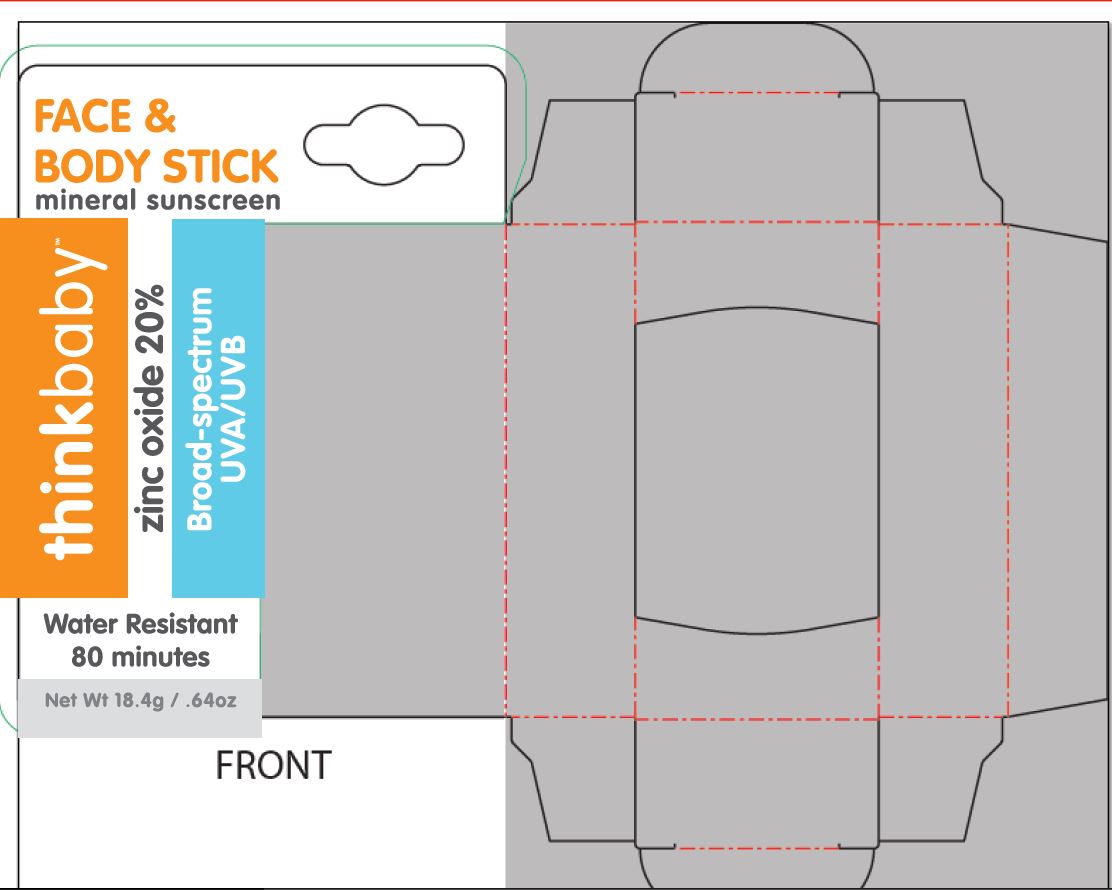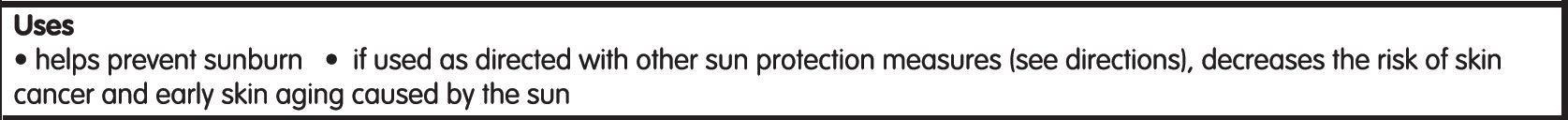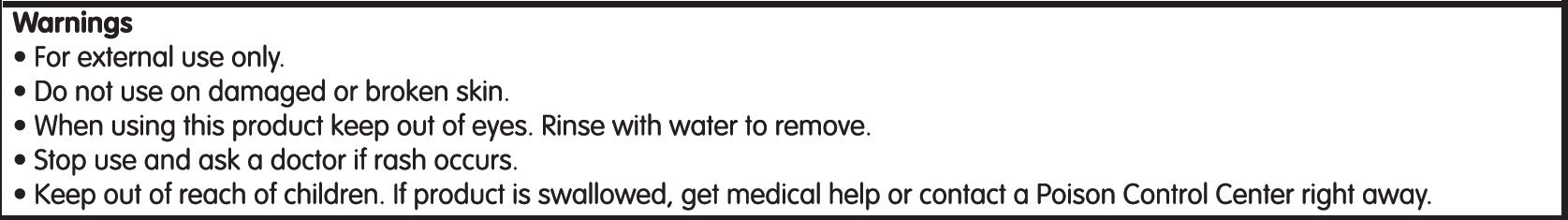 DRUG LABEL: Think Baby SPF 30
NDC: 62932-264 | Form: STICK
Manufacturer: Private Label Select Ltd CO
Category: otc | Type: HUMAN OTC DRUG LABEL
Date: 20220104

ACTIVE INGREDIENTS: ZINC OXIDE 20 g/100 g
INACTIVE INGREDIENTS: .DELTA.-TOCOPHEROL; WHITE WAX; SHEA BUTTER; SUNFLOWER OIL; CARNAUBA WAX; .ALPHA.-TOCOPHEROL, D-; .BETA.-TOCOPHEROL; COCONUT OIL; COCOA BUTTER; CANDELILLA WAX; ALOE VERA LEAF; .GAMMA.-TOCOPHEROL; CASTOR OIL

Think Operations, Think Baby SPF 30